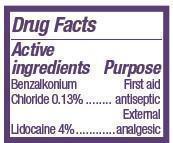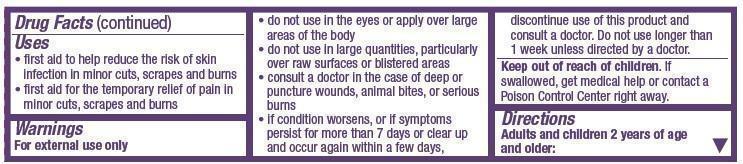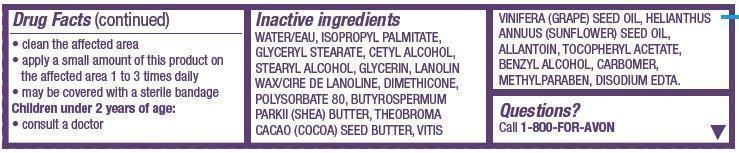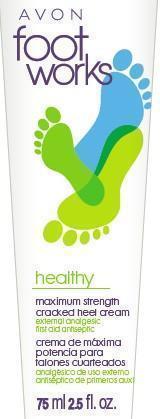 DRUG LABEL: Footworks
NDC: 10096-0284 | Form: CREAM
Manufacturer: New Avon LLC
Category: otc | Type: HUMAN OTC DRUG LABEL
Date: 20210901

ACTIVE INGREDIENTS: BENZALKONIUM CHLORIDE 1.3 mg/1 mL; LIDOCAINE 40 mg/1 mL
INACTIVE INGREDIENTS: WATER

AVON Footworks Maximum Strength Cracked Heel

Active ingredients

Benzalkonium Chloride 0.13%........

Lidocaine 4%............

Purpose

........First aid antiseptic

............External analgesic

Uses

• first aid to help reduce the risk of skin infection in minor cuts, scrapes and burns

• first aid for the temporary relief of pain in minor cuts, scrapes and burns

Warnings

For external use only

- do not use in the eyes or apply over large areas of the body
- do not use in large quantities, particularly over raw surfaces or blistered areas
- consult a doctor in the case of deep or puncture wounds, animal bites, or serious burns
- if condition worsens, or if symptoms persist for more than 7 days or clear up and occur again within a few days, discontinue use of this product and consult a doctor. Do not use longer than 1 week unless directed by a doctor.

Keep out of reach of children. If swallowed, get medical help or contact a Poison Control Center right away.

Directions

Adults and children 2 years of age and older:

• clean the affected area

• apply a small amount of this product on the affected area 1 to 3 times daily

• may be covered with a sterile bandage

Children under 2 years of age:

• consult a doctor

Inactive ingredients

WATER/EAU, ISOPROPYL PALMITATE, GLYCERYL STEARATE, CETYL ALCOHOL, STEARYL ALCOHOL, GLYCERIN, LANOLIN WAX/CIRE DE LANOLINE, DIMETHICONE, POLYSORBATE 80, BUTYROSPERMUM PARKII (SHEA) BUTTER, THEOBROMA CACAO (COCOA) SEED BUTTER, VITISVINIFERA (GRAPE) SEED OIL, HELIANTHUS ANNUUS (SUNFLOWER) SEED OIL, ALLANTOIN, TOCOPHERYL ACETATE, BENZYL ALCOHOL, CARBOMER, METHYLPARABEN, DISODIUM EDTA.

Questions?

Call 1-800-FOR-AVON